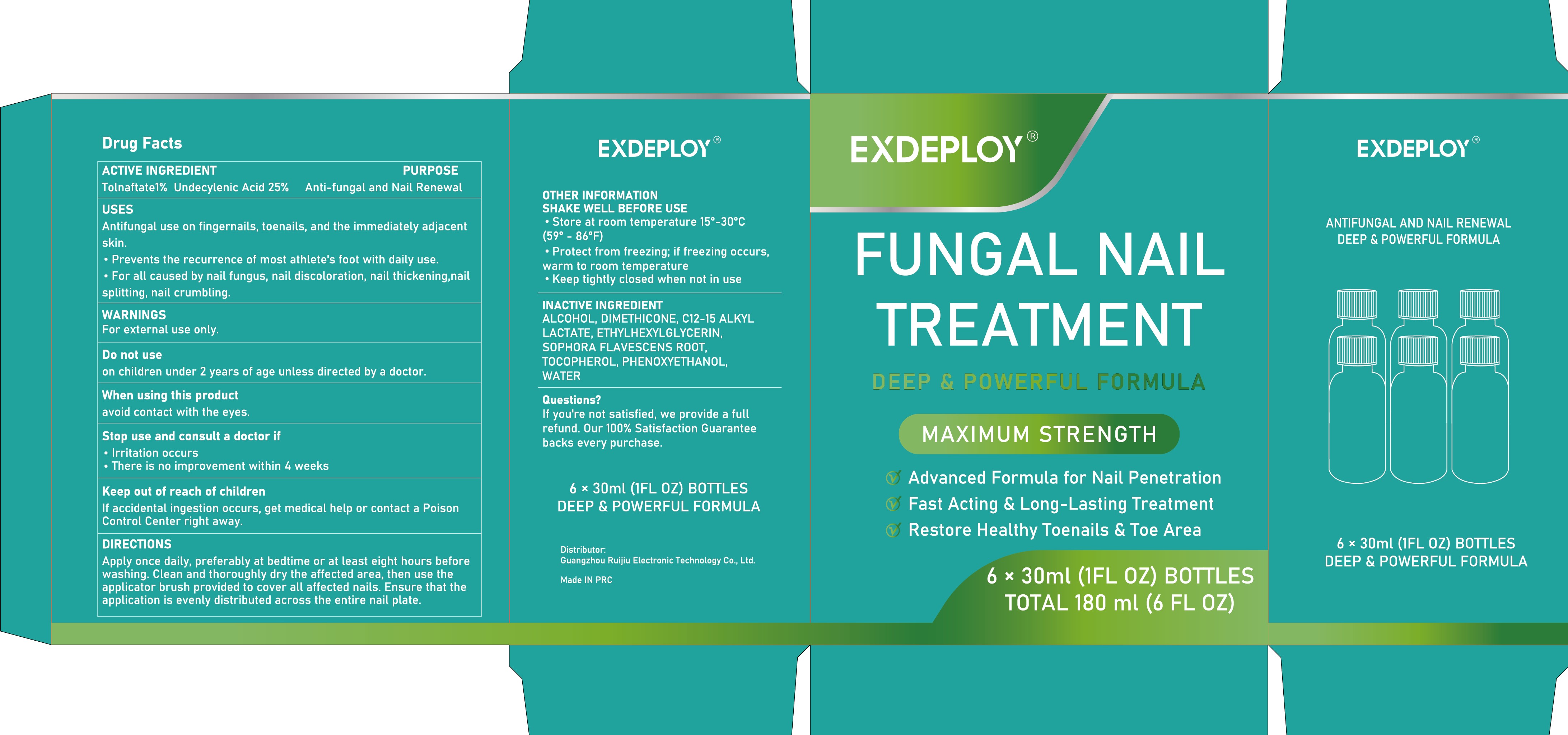 DRUG LABEL: FUNGAL NAIL TREATMENT MAXIMUM STRENGTH Liquid
NDC: 83767-003 | Form: LIQUID
Manufacturer: Guangzhou Ruijiu Electronic Technology Co., Ltd.
Category: otc | Type: HUMAN OTC DRUG LABEL
Date: 20241219

ACTIVE INGREDIENTS: TOLNAFTATE 1 g/100 mL; UNDECYLENIC ACID 25 g/100 mL
INACTIVE INGREDIENTS: PHENOXYETHANOL; SOPHORA FLAVESCENS ROOT; TOCOPHEROL; WATER; DIMETHICONE; C12-15 ALKYL LACTATE; ETHYLHEXYLGLYCERIN; ALCOHOL

FUNGAL NAIL TREATMENT MAXIMUM STRENGTH LIQUID

FUNGAL NAIL TREATMENT MAXIMUM STRENGTH LIQUID

ACTIVE INGREDIENT

TOLNAFTATE 1%
UNDECYLENIC ACID 25%

PURPOSE

Anti-fungal and Nail Renewal

INDICATIONS AND USAGE

Antifungal use on fingernails, toenails, and the immediately adjacentskin.
·Prevents the recurrence of most athlete's foot with daily use.

·For all caused by nail fungus, nail discoloration, nail thickening,nailsplitting, nail crumbling.

WARNINGS

For external use only.

DO NOT USE

on children under 2 years of age unless directed by a doctor

WHEN USING

avoid contact with the eyes

STOP USE

Irritation occurs
There is no improvement within 4 weeks

KEEP OUT OF REACH OF CHILDREN

If accidental ingestion occurs, get medical help or contact a PoisonControl Center right away.

DOSAGE AND ADMINISTRATION

Apply once daily, preferably at bedtime or at least eight hours before
washing. Clean and thoroughly dry the affected area, then use the
applicator brush provided to cover all affected nails. Ensure that the
application is evenly distributed across the entire nail plate.

STORAGE AND HANDLING

OTHER INFORMATIONSHAKE WELL BEFORE USEStore at room temperature 15°-30°C(59°- 86°F)
。Protect from freezing; if freezing occurs.warm to room temperatureKeep tightly closed when not in use

INACTIVE INGREDIENT

ALCOHOL
DIMETHICONE
C12-15 ALKYL LACTATE
ETHYLHEXYLGLYCERIN
TOCOPHEROL
SOPHORA FLAVESCENS ROOT
PHENOXYETHANOL
WATER